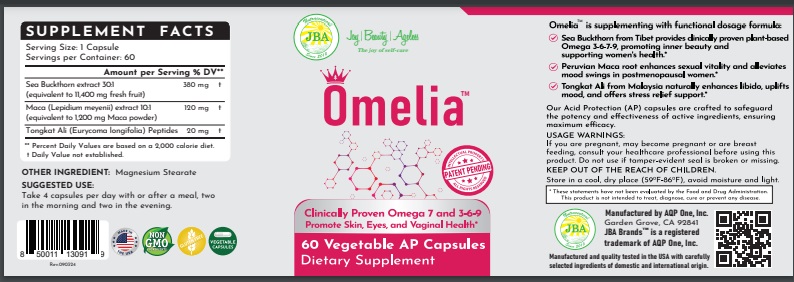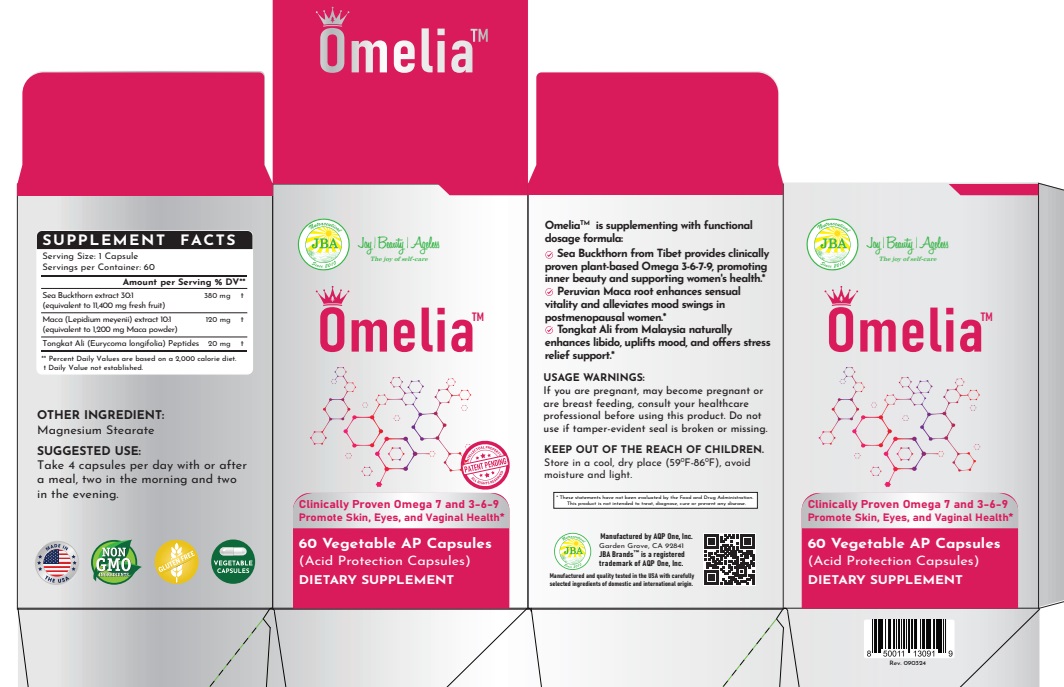 DRUG LABEL: JBA Omelia
NDC: 13411-857 | Form: CAPSULE
Manufacturer: Advanced Pharmaceutical Services, Inc. Dba Affordable Quality Pharmaceuticals
Category: otc | Type: HUMAN OTC DRUG LABEL
Date: 20250331

ACTIVE INGREDIENTS: HIPPOPHAE RHAMNOIDES WHOLE 380 mg/1 1; LEPIDIUM MEYENII ROOT 120 mg/1 1; EURYCOMA LONGIFOLIA ROOT 20 mg/1 1
INACTIVE INGREDIENTS: MAGNESIUM STEARATE

Identity

Dietary supplement

Direction

Take 4 capsules per day with or after a meal, two in the morning and two in the evening.

Safe handling warning

OmeliaTM

Clinically Proven Omega 7 and 3-6-9 Promote Skin, Eyes, and Vaginal Health*

OmeliaTM is supplementing with functional dosage formula:

- Sea Buckthorn from Tibet provides clinically proven plant-based Omega 3-6-7-9, promoting inner beauty and supporting women’s health.*
- Peruvian Maca root enhances sexual vitality and alleviates mood swings in postmenopausal women.*
- Tongkat Ali from Malaysia naturally enhances libido, uplifts mood, and offers stress relief support.*

* These statements have not been evaluated by the Food & Drug Administration. This product is not intended to diagnose, treat, cure, or prevent any disease.

PRECAUTIONS

If you are pregnant, may become pregnant or are breast feeding, consult your healthcare professional before using this product. Do not use if tamper-evident seal is broken or missing.

Keep Out of The Reach of Children.
Store in a cool, dry place (59oF-86oF), avoid moisture and light.

WARNINGS

Other Ingredients

Maltodextrin, Magnesium Stearate